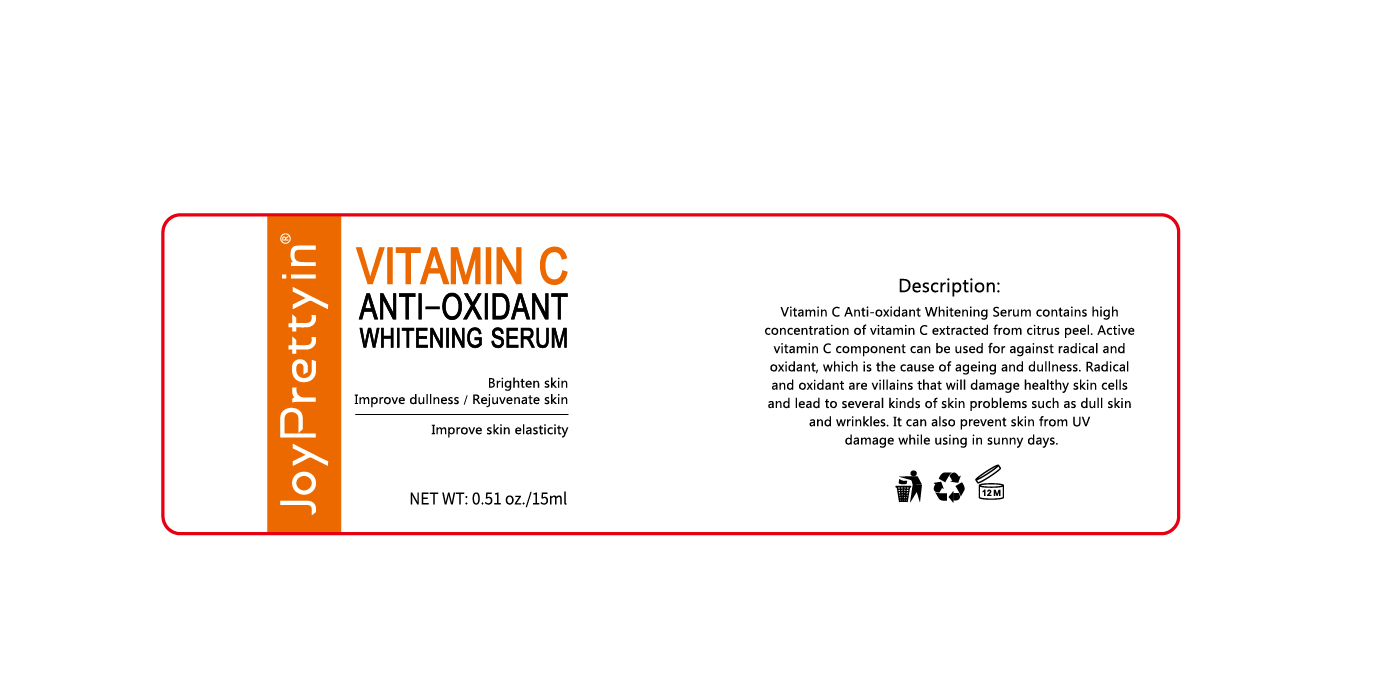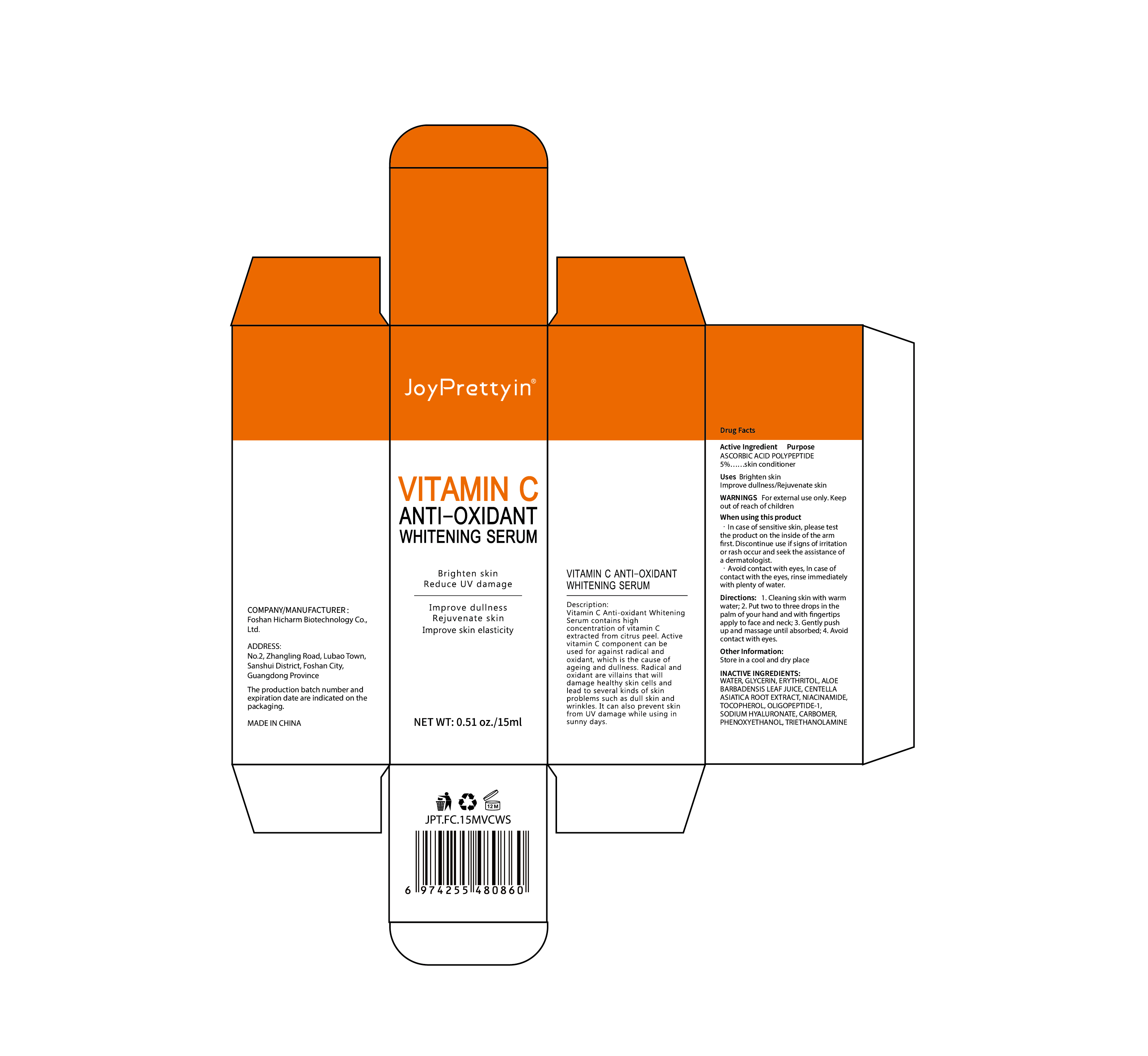 DRUG LABEL: JoyPretty VITAMIN CANTI-OXIDANTWHITENING SERUM
NDC: 84186-007 | Form: LIQUID
Manufacturer: Guangzhou Bonnieco Cosmetics Co., Ltd
Category: otc | Type: HUMAN OTC DRUG LABEL
Date: 20240329

ACTIVE INGREDIENTS: GLYCERIN 8 g/100 mL
INACTIVE INGREDIENTS: NIACINAMIDE; PHENOXYETHANOL; TOCOPHEROL; ALOE VERA LEAF; WATER; ASCORBIC ACID; CENTELLA ASIATICA ROOT; OLIGOPEPTIDE-10; HYALURONATE SODIUM; TROLAMINE; ERYTHRITOL; CARBOMER HOMOPOLYMER, UNSPECIFIED TYPE

84186-007

Active Ingredient

GLYCERIN 1%

Purpose

whiten (the skin or teeth)

Use

Brighten skin lmprove dullness/Rejuvenate skin

Warnings

For external use only.Keepout of reach of children

Do not use

In case of sensitive skin, please testthe product on the inside of the armfirst. Discontinue use if signs of irritationor rash occur and seek the assistance ofa dermatologist. · Avoid contact with eyes, In case ofcontact with the eyes, rinse immediatelywith plenty of water.Directions: 1.Cleaning skin with warmwater; 2.Put two to three drops in thepalm of your hand and with fingertipsapply to face and neck; 3.Gently pushup and massage until absorbed; 4.Avoidcontact with eyes.

When Using

In case of contact with the eyes, rinse immediately with plenty of water.

Stop Use

If discomfort arises, please immediately stop using the product and seek the assistance of a dermatologist.

Ask Doctor

If discomfort arises, please immediately stop using the product and seek the assistance of a dermatologist.

Keep Oot Of Reach Of Children

Keep out of reach of children. If swallowed call emergency services.

Directions

1.Cleaning skin with warm water;
2. Put two to three drops in thepalm of your hand and withfingertips apply to face and neck;
3.Gently push up and massageuntil absorbed;
4.Avoid contact with eyes.

Other information

Store in a cool and dry place

Inactive ingredients

WATER, GLYCERIN, ERYTHRITOL, ASCORBIC ACID POLYPEPTIDE, ALOE BARBADENSIS LEAF JUICE, CENTELLA ASIATICA ROOT EXTRACT, NIACINAMIDE, TOCOPHEROL, OLIGOPEPTIDE-1, SODIUM HYALURONATE, CARBOMER, PHENOXYETHANOL, TRIETHANOLAMINE